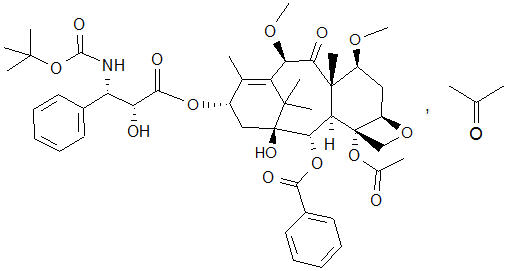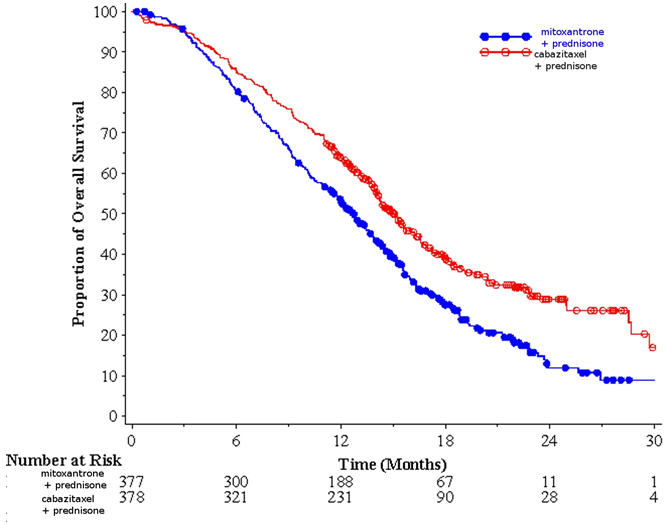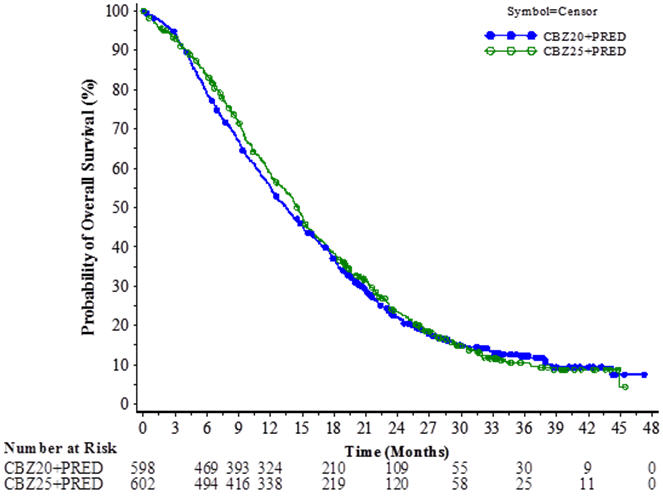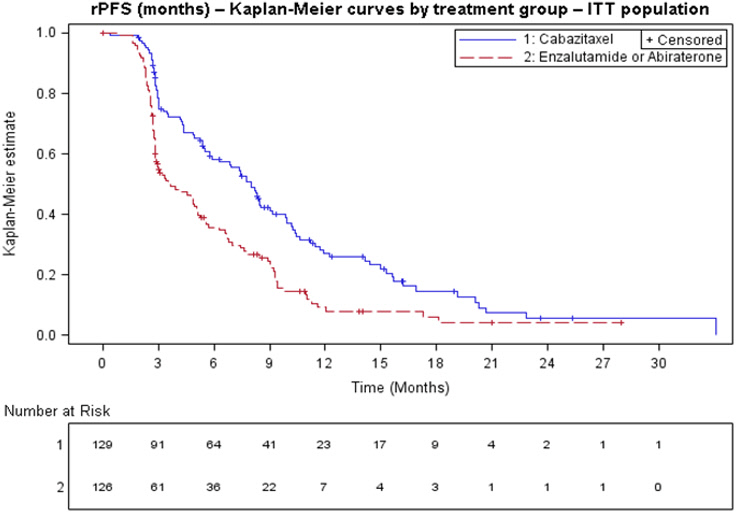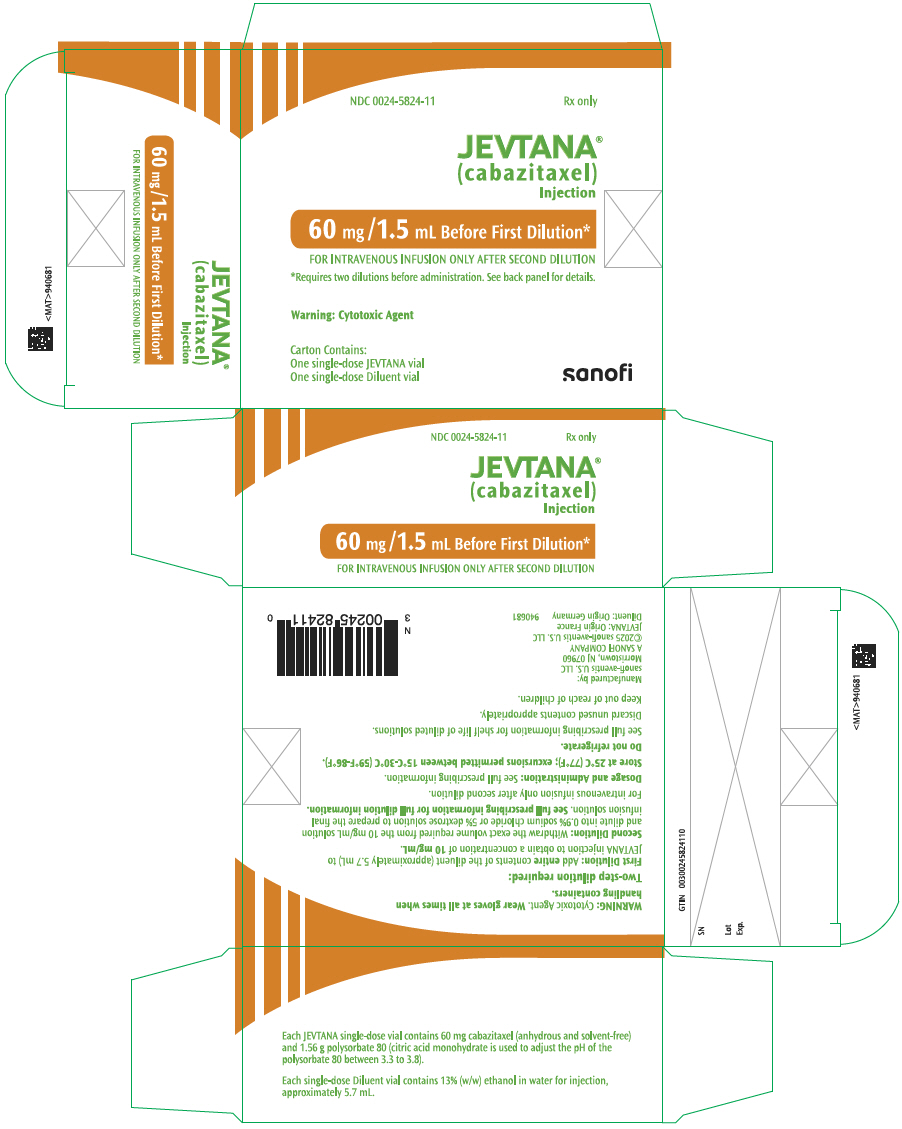 DRUG LABEL: Jevtana
NDC: 0024-5824 | Form: KIT | Route: INTRAVENOUS
Manufacturer: Sanofi-Aventis U.S. LLC
Category: prescription | Type: HUMAN PRESCRIPTION DRUG LABEL
Date: 20251007

ACTIVE INGREDIENTS: CABAZITAXEL 60 mg/1.5 mL
INACTIVE INGREDIENTS: POLYSORBATE 80 1.56 g/1.5 mL; ALCOHOL; WATER

HIGHLIGHTS OF PRESCRIBING INFORMATION

These highlights do not include all the information needed to use JEVTANA safely and effectively. See full prescribing information for JEVTANA.
JEVTANA® (cabazitaxel) injection, for intravenous use
Initial U.S. Approval: 2010

WARNING: NEUTROPENIA AND HYPERSENSITIVITY

See full prescribing information for complete boxed warning.

- Neutropenic deaths have been reported. Obtain frequent blood counts to monitor for neutropenia. JEVTANA is contraindicated in patients with neutrophil counts of ≤1,500 cells/mm^3. Primary prophylaxis with G-CSF is recommended in patients with high-risk clinical features. Consider primary prophylaxis with G-CSF in all patients receiving a dose of 25 mg/m^2 (4, 5.1, 5.2)
- Severe hypersensitivity can occur and may include generalized rash/erythema, hypotension and bronchospasm. Discontinue JEVTANA immediately if severe reactions occur and administer appropriate therapy. (2.1, 5.2)
- Contraindicated if history of severe hypersensitivity reactions to cabazitaxel or to drugs formulated with polysorbate 80. (4)

1 INDICATIONS AND USAGE

JEVTANA is a microtubule inhibitor indicated in combination with prednisone for treatment of patients with metastatic castration-resistant prostate cancer previously treated with a docetaxel-containing treatment regimen. (1)

2 DOSAGE AND ADMINISTRATION

Recommended Dose: JEVTANA 20 mg/m^2 administered every three weeks as a one-hour intravenous infusion in combination with oral prednisone 10 mg administered daily throughout JEVTANA treatment. (2.1)

A dose of 25 mg/m^2 can be used in select patients at the discretion of the treating healthcare provider. (2.1, 5.1, 5.2, 6.1, 14)

- JEVTANA requires two dilutions prior to administration. (2.5)
- Use the entire contents of the accompanying diluent to achieve a concentration of 10 mg/mL JEVTANA. (2.5)
- PVC equipment should not be used. (2.5)
- Premedication Regimen: Administer intravenously 30 minutes before each dose of JEVTANA:
  - Antihistamine (dexchlorpheniramine 5 mg or diphenhydramine 25 mg or equivalent antihistamine)
  - Corticosteroid (dexamethasone 8 mg or equivalent steroid)
  - H2 antagonist (2.1)
  Antiemetic prophylaxis (oral or intravenous) is recommended as needed. (2.1)
- Dosage Modifications: See full prescribing information (2.2, 2.3, 2.4)

3 DOSAGE FORMS AND STRENGTHS

- Single dose vial 60 mg/1.5 mL, supplied with diluent (5.7 mL) for JEVTANA (3)

4 CONTRAINDICATIONS

- Neutrophil counts of ≤1,500/mm^3 (2.2, 4)
- History of severe hypersensitivity to JEVTANA or polysorbate 80 (4)
- Severe hepatic impairment (Total Bilirubin >3 × ULN) (4)

5 WARNINGS AND PRECAUTIONS

- Bone marrow suppression (particularly neutropenia) and its clinical consequences (febrile neutropenia, neutropenic infections, and death): Monitor blood counts frequently to determine if dosage modification or initiation of G-CSF is needed. Closely monitor patients with hemoglobin <10 g/dL. (2.2, 4, 5.1)
- Increased toxicities in elderly patients: Patients ≥65 years of age were more likely to experience fatal outcomes and certain adverse reactions, including neutropenia and febrile neutropenia. Monitor closely. (5.2, 8.5)
- Hypersensitivity: Severe hypersensitivity reactions can occur. Premedicate with corticosteroids and H2 antagonists. Discontinue infusion immediately if hypersensitivity is observed and treat as indicated. (4, 5.3)
- Gastrointestinal disorders: Nausea, vomiting, and diarrhea may occur. Mortality related to diarrhea has been reported. Rehydrate and treat with antiemetics and antidiarrheals as needed. If experiencing Grade ≥3 diarrhea, dosage should be modified. (2.2) Deaths have occurred due to gastrointestinal hemorrhage, perforation and neutropenic enterocolitis. Delay or discontinue JEVTANA and treat as indicated. (5.4)
- Renal failure, including cases with fatal outcomes, has been reported. Identify cause and manage aggressively. (5.5)
- Urinary disorders including cystitis: Cystitis, radiation cystitis, and hematuria may occur. Monitor patients who previously received pelvic radiation for signs and symptoms of cystitis. Interrupt or discontinue JEVTANA and provide medical or surgical supportive care, as needed, in patients experiencing severe hemorrhagic cystitis. (5.6)
- Respiratory disorders: Interstitial pneumonia/pneumonitis, interstitial lung disease and acute respiratory distress syndrome, including fatal outcomes, have been reported. Delay or discontinue JEVTANA and treat as indicated. (5.7)
- Hepatic impairment: Administer JEVTANA at a dose of 20 mg/m^2 in patients with mild hepatic impairment. Administer JEVTANA at a dose of 15 mg/m^2 in patients with moderate hepatic impairment. (2.3, 5.8)
- Embryo-fetal toxicity: JEVTANA can cause fetal harm and loss of pregnancy. Advise males with female partners of reproductive potential to use effective contraception. (5.9, 8.1, 8.3)

6 ADVERSE REACTIONS

Most common all grades adverse reactions and laboratory abnormalities (≥10%) with JEVTANA 20 mg/m^2 or 25 mg/m^2 are neutropenia, anemia, diarrhea, nausea, fatigue, asthenia, vomiting, hematuria, constipation, decreased appetite, back pain, and abdominal pain. (6)

To report SUSPECTED ADVERSE REACTIONS, contact sanofi-aventis U.S. LLC at 1-800-633-1610 or FDA at 1-800-FDA-1088 or www.fda.gov/medwatch.

7 DRUG INTERACTIONS

Avoid coadministration of JEVTANA with strong CYP3A inhibitors. If patients require coadministration of a strong CYP3A inhibitor, consider a 25% JEVTANA dose reduction. (2.4, 7.1, 12.3)

FULL PRESCRIBING INFORMATION

WARNING: NEUTROPENIA AND HYPERSENSITIVITY

Neutropenia: Neutropenic deaths have been reported. Monitor for neutropenia with frequent blood cell counts. JEVTANA is contraindicated in patients with neutrophil counts of ≤1,500 cells/mm^3. Primary prophylaxis with G-CSF is recommended in patients with high-risk clinical features. Consider primary prophylaxis with G-CSF in all patients receiving a dose of 25 mg/m^2 [see Contraindications (4) and Warnings and Precautions (5.1, 5.2)].

Severe hypersensitivity: Severe hypersensitivity reactions can occur and may include generalized rash/erythema, hypotension and bronchospasm. Severe hypersensitivity reactions require immediate discontinuation of the JEVTANA infusion and administration of appropriate therapy. Patients should receive premedication. JEVTANA is contraindicated in patients who have a history of severe hypersensitivity reactions to cabazitaxel or to other drugs formulated with polysorbate 80 [see Dosage and Administration (2.1), Contraindications (4), and Warnings and Precautions (5.3)].

1 INDICATIONS AND USAGE

JEVTANA® is indicated in combination with prednisone for the treatment of patients with metastatic castration-resistant prostate cancer previously treated with a docetaxel-containing treatment regimen.

2 DOSAGE AND ADMINISTRATION

2.1 Dosing Information

The recommended dose of JEVTANA is based on calculation of the Body Surface Area (BSA), and is 20 mg/m^2 administered as a one-hour intravenous infusion every three weeks in combination with oral prednisone 10 mg administered daily throughout JEVTANA treatment.

A dose of 25 mg/m^2 can be used in select patients at the discretion of the treating healthcare provider [see Warnings and Precautions (5.1, 5.2), Adverse Reactions (6.1), and Clinical Studies (14)].

Primary prophylaxis with G-CSF is recommended in patients with high-risk clinical features. Consider primary prophylaxis with G-CSF in all patients receiving a dose of 25 mg/m^2 [see Contraindications (4) and Warnings and Precautions (5.1, 5.2)].

Premedicate at least 30 minutes prior to each dose of JEVTANA with the following intravenous medications to reduce the risk and/or severity of hypersensitivity [see Warnings and Precautions (5.3)]:

- antihistamine (dexchlorpheniramine 5 mg, or diphenhydramine 25 mg or equivalent antihistamine),
- corticosteroid (dexamethasone 8 mg or equivalent steroid),
- H2 antagonist.

Antiemetic prophylaxis is recommended and can be given orally or intravenously as needed [see Warnings and Precautions (5.3)].

JEVTANA injection single-dose vial requires two dilutions prior to administration [see Dosage and Administration (2.5)].

2.2 Dose Modifications for Adverse Reactions

Reduce or discontinue JEVTANA dosing for adverse reactions as described in Table 1.

Table 1: Recommended Dosage Modifications for Adverse Reactions in Patients Treated with JEVTANA
Toxicity | Dosage Modification
Prolonged grade ≥3 neutropenia (greater than 1 week) despite appropriate medication including granulocyte-colony stimulating factor (G-CSF) | Delay treatment until neutrophil count is >1,500 cells/mm^3, then reduce dosage of JEVTANA by one dose level. Use G-CSF for secondary prophylaxis.
Febrile neutropenia or neutropenic infection | Delay treatment until improvement or resolution, and until neutrophil count is >1,500 cells/mm^3, then reduce dosage of JEVTANA by one dose level. Use G-CSF for secondary prophylaxis.
Grade ≥3 diarrhea or persisting diarrhea despite appropriate medication, fluid and electrolytes replacement | Delay treatment until improvement or resolution, then reduce dosage of JEVTANA by one dose level.
Grade 2 peripheral neuropathy | Delay treatment until improvement or resolution, then reduce dosage of JEVTANA by one dose level.
Grade ≥3 peripheral neuropathy | Discontinue JEVTANA.

Patients at a 20 mg/m^2 dose who require dose reduction should decrease dosage of JEVTANA to 15 mg/m^2 [see Adverse Reactions (6.1)].

Patients at a 25 mg/m^2 dose who require dose reduction should decrease dosage of JEVTANA to 20 mg/m^2. One additional dose reduction to 15 mg/m^2 may be considered [see Adverse Reactions (6.1)].

2.3 Dose Modifications for Hepatic Impairment

- Mild hepatic impairment (total bilirubin >1 to ≤1.5 × Upper Limit of Normal (ULN) or AST >1.5 × ULN): Administer JEVTANA at a dose of 20 mg/m^2.
- Moderate hepatic impairment (total bilirubin >1.5 to ≤3 × ULN and AST = any): Administer JEVTANA at a dose of 15 mg/m^2 based on tolerability data in these patients; however, the efficacy of this dose is unknown.
- Severe hepatic impairment (total bilirubin >3 × ULN): JEVTANA is contraindicated in patients with severe hepatic impairment [see Warning and Precautions (5.8) and Clinical Pharmacology (12.3)].

2.4 Dose Modifications for Use with Strong CYP3A Inhibitors

Concomitant drugs that are strong CYP3A inhibitors (e.g., ketoconazole, itraconazole, clarithromycin, atazanavir, indinavir, nefazodone, nelfinavir, ritonavir, saquinavir, telithromycin, voriconazole) may increase plasma concentrations of cabazitaxel. Avoid the coadministration of JEVTANA with these drugs. If patients require coadministration of a strong CYP3A inhibitor, consider a 25% JEVTANA dose reduction [see Drug Interactions (7.1) and Clinical Pharmacology (12.3)].

2.5 Preparation and Administration

JEVTANA is a hazardous anticancer drug. Follow applicable special handling and disposal procedures [see References (15)]. If JEVTANA first diluted solution, or second (final) dilution for intravenous infusion should come into contact with the skin or mucous, immediately and thoroughly wash with soap and water.

Do not use PVC infusion containers or polyurethane infusions sets for preparation and administration of JEVTANA infusion solution.

JEVTANA should not be mixed with any other drugs.

Preparation

Read this entire section carefully before mixing and diluting. JEVTANA requires two dilutions prior to administration. Follow the preparation instructions provided below, as improper preparation may lead to overdose [see Overdosage (10)].

Note: Both the JEVTANA injection and the diluent vials contain an overfill to compensate for liquid loss during preparation. This overfill ensures that after dilution with the entire contents of the accompanying diluent, there is an initial diluted solution containing 10 mg/mL JEVTANA.

Inspect the JEVTANA injection and supplied diluent vials. The JEVTANA injection is a clear yellow to brownish-yellow viscous solution.

Step 1 – first dilution

Each vial of JEVTANA (cabazitaxel) 60 mg/1.5 mL must first be mixed with the entire contents of supplied diluent. Once reconstituted, the resultant solution contains 10 mg/mL of JEVTANA.

When transferring the diluent, direct the needle onto the inside wall of JEVTANA vial and inject slowly to limit foaming. Remove the syringe and needle and gently mix the initial diluted solution by repeated inversions for at least 45 seconds to assure full mixing of the drug and diluent. Do not shake.

Let the solution stand for a few minutes to allow any foam to dissipate, and check that the solution is homogeneous and contains no visible particulate matter. It is not required that all foam dissipate prior to continuing the preparation process.

The resulting initial diluted JEVTANA solution (cabazitaxel 10 mg/mL) requires further dilution before administration. The second dilution should be done immediately (within 30 minutes) to obtain the final infusion as detailed in Step 2.

Step 2 – second (final) dilution

Withdraw the recommended dose from the JEVTANA solution containing 10 mg/mL as prepared in Step 1 using a calibrated syringe and further dilute into a sterile 250 mL PVC-free container of either 0.9% sodium chloride solution or 5% dextrose solution for infusion. If a dose greater than 65 mg of JEVTANA is required, use a larger volume of the infusion vehicle so that a concentration of 0.26 mg/mL JEVTANA is not exceeded. The concentration of the JEVTANA final infusion solution should be between 0.10 mg/mL and 0.26 mg/mL.

Remove the syringe and thoroughly mix the final infusion solution by gently inverting the bag or bottle.

As the final infusion solution is supersaturated, it may crystallize over time. Do not use if this occurs and discard.

Fully prepared JEVTANA infusion solution (in either 0.9% sodium chloride solution or 5% dextrose solution) should be used within 8 hours at ambient temperature (including the one-hour infusion), or for a total of 24 hours (including the one-hour infusion) under the refrigerated conditions.

Discard any unused portion.

Administration

Inspect visually for particulate matter, any crystals and discoloration prior to administration. If the JEVTANA first diluted solution or second (final) infusion solution is not clear or appears to have precipitation, it should be discarded.

Use an in-line filter of 0.22 micrometer nominal pore size (also referred to as 0.2 micrometer) during administration.

The final JEVTANA infusion solution should be administered intravenously as a one-hour infusion at room temperature.

3 DOSAGE FORMS AND STRENGTHS

JEVTANA (cabazitaxel) injection is supplied as a kit consisting of the following:

- Cabazitaxel injection: 60 mg/1.5 mL; a clear yellow to brownish-yellow viscous solution
- Diluent: 5.7 mL of 13% (w/w) ethanol in water; a clear colorless solution

4 CONTRAINDICATIONS

JEVTANA is contraindicated in patients with:

- neutrophil counts of ≤1,500/mm^3 [see Warnings and Precautions (5.1)]
- history of severe hypersensitivity reactions to cabazitaxel or to other drugs formulated with polysorbate 80 [see Warnings and Precautions (5.3)]
- severe hepatic impairment (total bilirubin >3 × ULN) [see Warnings and Precautions (5.8)]

5 WARNINGS AND PRECAUTIONS

5.1 Bone Marrow Suppression

JEVTANA is contraindicated in patients with neutrophils ≤1,500/mm^3 [see Contraindications (4)]. Closely monitor patients with hemoglobin <10 g/dL.

Bone marrow suppression manifested as neutropenia, anemia, thrombocytopenia and/or pancytopenia may occur. Neutropenic deaths have been reported.

TROPIC Trial (JEVTANA 25 mg/m^2)

In the TROPIC trial with G-CSF administered only at the investigator's discretion, 5 patients (1.3%) died from neutropenic infection (sepsis or septic shock); 4 of these patients died in the first 30 days of treatment. One additional patient's death was attributed to neutropenia without a documented infection. Twenty-two (6%) patients discontinued JEVTANA treatment due to neutropenia, febrile neutropenia, infection, or sepsis. Grade 3–4 neutropenia occurred in 82% of patients treated with JEVTANA in the randomized trial [see Adverse Reactions (6.1)].

PROSELICA Trial (comparison of JEVTANA 20 mg/m^2 versus 25 mg/m^2)

In the PROSELICA trial comparing two doses of JEVTANA, primary prophylaxis with G-CSF was not allowed, but could be administered after development of neutropenia at investigators discretion. Eight patients (1%) on the 20 mg/m^2 arm and 15 patients (3%) on the 25 mg/m^2 arm died from infection; of these, 4 deaths on the 20 mg/m^2 arm and 8 deaths on the 25 mg/m^2 arm occurred within the first 30 days of treatment. Clinically important neutropenia-related events occurred and included febrile neutropenia (2.1% on 20 mg/m^2 arm and 9.2% on 25 mg/m^2 arm), neutropenic infection/sepsis (2.1% on 20 mg/m^2 arm and 6.4% on 25 mg/m^2 arm), and neutropenic deaths (0.3% on 20 mg/m^2 arm and 0.7% on 25 mg/m^2 arm).

Fewer patients receiving JEVTANA 20 mg/m^2 were reported to have infectious adverse reactions. Grade 1–4 infections were experienced by 160 patients (28%) on the 20 mg/m^2 arm and 227 patients (38%) on the 25 mg/m^2 arm. Grade 3–4 infections were experienced by 57 patients (10%) on the 20 mg/m^2 arm and 120 patients (20%) on the 25 mg/m^2 arm. Noninferiority for overall survival was demonstrated between these two arms [see Adverse Reactions (6.1)].

CARD Trial (JEVTANA 25 mg/m^2 + primary prophylaxis G-CSF)

In the CARD trial where JEVTANA 25 mg/m^2 was administered with primary prophylaxis of G-CSF, 1 patient (0.8%) died from sepsis within the first 30 days of treatment. Grade 1–4 neutropenia-related adverse reactions were experienced in 33 patients (26%). Grade 3–4 neutropenias were experienced by 26 patients (21%). Clinically important neutropenia-related events occurred and included febrile neutropenia (3.2%), neutropenic infection/sepsis (0.8%) and neutropenic deaths (0.8%) [see Adverse Reactions (6.1)].

Based on guidelines for the use of G-CSF and the adverse reactions profile of JEVTANA, primary prophylaxis with G-CSF is recommended in patients with high-risk clinical features (older patients, poor performance status, previous episodes of febrile neutropenia, extensive prior radiation ports, poor nutritional status, or other serious comorbidities) that predispose them to increased complications from prolonged neutropenia. Consider primary prophylaxis with G-CSF in all patients receiving JEVTANA 25 mg/m^2.

Monitoring of complete blood counts is essential on a weekly basis during cycle 1 and before each treatment cycle thereafter so that the dose can be adjusted, if needed [see Dosage and Administration (2.2)].

5.2 Increased Toxicities in Elderly Patients

In a randomized trial (TROPIC), 2% of patients (3/131) <65 years of age and 6% (15/240) ≥65 years of age died of causes other than disease progression within 30 days of the last JEVTANA dose. Patients ≥65 years of age are more likely to experience certain adverse reactions, including neutropenia and febrile neutropenia. The incidence of the following grade 3–4 adverse reactions was higher in patients ≥65 years of age compared to younger patients; neutropenia (87% vs 74%), and febrile neutropenia (8% vs 6%).

In a randomized clinical trial (PROSELICA) comparing two doses of JEVTANA, deaths due to infection within 30 days of starting JEVTANA occurred in 0.7% (4/580) patients on the 20 mg/m^2 arm and 1.3% (8/595) patients on the 25 mg/m^2 arm; all of these patients were >60 years of age.

In PROSELICA, on the 20 mg/m^2 arm, 3% (5/178) of patients <65 years of age and 2% (9/402) ≥65 years of age died of causes other than disease progression within 30 days of the last JEVTANA dose. On the 25 mg/m^2 arm, 2% (3/175) patients <65 years of age and 5% (20/420) ≥65 years of age died of causes other than disease progression within 30 days of the last JEVTANA dose [see Adverse Reactions (6) and Use in Specific Populations (8.5)].

In CARD, a death due to infection within 30 days of starting JEVTANA occurred in 0.8% (1/126) patient who was >75 years of age. There were 2.4% (3/126) of patients who died of causes other than disease progression within 30 days of the last JEVTANA dose; all of these patients were >75 years of age.

5.3 Hypersensitivity Reactions

Hypersensitivity reactions may occur within a few minutes following the initiation of the infusion of JEVTANA, thus facilities and equipment for the treatment of hypotension and bronchospasm should be available. Severe hypersensitivity reactions can occur and may include generalized rash/erythema, hypotension and bronchospasm.

Premedicate all patients prior to the initiation of the infusion of JEVTANA [see Dosage and Administration (2.1)]. Observe patients closely for hypersensitivity reactions, especially during the first and second infusions. Severe hypersensitivity reactions require immediate discontinuation of the JEVTANA infusion and appropriate therapy. JEVTANA is contraindicated in patients with a history of severe hypersensitivity reactions to cabazitaxel or to other drugs formulated with polysorbate 80 [see Contraindications (4)].

5.4 Gastrointestinal Adverse Reactions

Nausea, vomiting and severe diarrhea, at times, may occur. Deaths related to diarrhea and electrolyte imbalance occurred in the randomized clinical trials. Intensive measures may be required for severe diarrhea and electrolyte imbalance. Antiemetic prophylaxis is recommended. Treat patients with rehydration, antidiarrheal or antiemetic medications as needed. Treatment delay or dosage reduction may be necessary if patients experience Grade ≥3 diarrhea [see Dosage and Administration (2.2)].

Gastrointestinal (GI) hemorrhage and perforation, ileus, enterocolitis, neutropenic enterocolitis, including fatal outcome, have been reported in patients treated with JEVTANA [see Adverse Reactions (6.2)]. Risk may be increased with neutropenia, age, steroid use, concomitant use of NSAIDs, antiplatelet therapy or anticoagulants, and patients with a prior history of pelvic radiotherapy, adhesions, ulceration and GI bleeding.

Abdominal pain and tenderness, fever, persistent constipation, diarrhea, with or without neutropenia, may be early manifestations of serious gastrointestinal toxicity and should be evaluated and treated promptly. JEVTANA treatment delay or discontinuation may be necessary.

The incidence of gastrointestinal adverse reactions is greater in the patients who have received prior radiation. In PROSELICA, diarrhea was reported in 41% (297/732) of patients who had received prior radiation and in 27% (118/443) of patients without prior radiation. Of the patients who had previously received radiation, more patients on the 25 mg/m^2 arm reported diarrhea, compared to patients on the 20 mg/m^2 arm.

5.5 Renal Failure

In the randomized clinical trial (TROPIC), renal failure of any grade occurred in 4% of the patients being treated with JEVTANA, including four cases with fatal outcome. Most cases occurred in association with sepsis, dehydration, or obstructive uropathy [see Adverse Reactions (6.1)]. Some deaths due to renal failure did not have a clear etiology. Appropriate measures should be taken to identify causes of renal failure and treat aggressively.

5.6 Urinary Disorders Including Cystitis

Cystitis, radiation cystitis, and hematuria, including that requiring hospitalization, has been reported with JEVTANA in patients who previously received pelvic radiation [see Adverse Reactions (6.2)]. In PROSELICA, cystitis and radiation cystitis were reported in 1.2% and 1.5% of patients who received prior radiation, respectively. Hematuria was reported in 19.4% of patients who received prior radiation and in 14.4% of patients who did not receive prior radiation. Cystitis from radiation recall may occur late in treatment with JEVTANA. Monitor patients who previously received pelvic radiation for signs and symptoms of cystitis while on JEVTANA. Interrupt or discontinue JEVTANA in patients experiencing severe hemorrhagic cystitis. Medical and/or surgical supportive treatment may be required to treat severe hemorrhagic cystitis.

5.7 Respiratory Disorders

Interstitial pneumonia/pneumonitis, interstitial lung disease and acute respiratory distress syndrome have been reported and may be associated with fatal outcome [see Adverse Reactions (6.2)]. Patients with underlying lung disease may be at higher risk for these events. Acute respiratory distress syndrome may occur in the setting of infection.

Interrupt JEVTANA if new or worsening pulmonary symptoms develop. Closely monitor, promptly investigate, and appropriately treat patients receiving JEVTANA. Consider discontinuation. The benefit of resuming JEVTANA treatment must be carefully evaluated.

5.8 Use in Patients with Hepatic Impairment

Cabazitaxel is extensively metabolized in the liver.

JEVTANA is contraindicated in patients with severe hepatic impairment (total bilirubin >3 × ULN) [see Contraindications (4)]. Dose should be reduced for patients with mild (total bilirubin >1 to ≤1.5 × ULN or AST >1.5 × ULN) and moderate (total bilirubin >1.5 to ≤3.0 × ULN and any AST) hepatic impairment, based on tolerability data in these patients [see Dosage and Administration (2.3) and Use in Specific Populations (8.7)]. Administration of JEVTANA to patients with mild and moderate hepatic impairment should be undertaken with caution and close monitoring of safety.

5.9 Embryo-Fetal Toxicity

Based on findings in animal reproduction studies and its mechanism of action, JEVTANA can cause fetal harm when administered to a pregnant woman [see Clinical Pharmacology (12.1)]. There are no available data in pregnant women to inform the drug-associated risk. In animal reproduction studies, intravenous administration of cabazitaxel in pregnant rats during organogenesis caused embryonic and fetal death at doses lower than the maximum recommended human dose (approximately 0.06 times the Cmax in patients at the recommended human dose). Advise males with female partners of reproductive potential to use effective contraception during treatment and for 4 months after the last dose of JEVTANA [see Use in Specific Populations (8.1, 8.3)].

6 ADVERSE REACTIONS

The following serious adverse reactions are discussed in greater detail in another section of the label:

- Bone Marrow Suppression [see Warnings and Precautions (5.1)]
- Increased Toxicities in Elderly Patients [see Warnings and Precautions (5.2)]
- Hypersensitivity Reactions [see Warnings and Precautions (5.3)]
- Gastrointestinal Adverse Reactions [see Warnings and Precautions (5.4)]
- Renal Failure [see Warnings and Precautions (5.5)]
- Urinary Disorders Including Cystitis [see Warnings and Precautions (5.6)]
- Respiratory Disorders [see Warnings and Precautions (5.7)]
- Use in Patients with Hepatic Impairment [see Warnings and Precautions (5.8)]

6.1 Clinical Trials Experience

Because clinical trials are conducted under widely varying conditions, the adverse reaction rates observed cannot be directly compared to rates in other trials and may not reflect the rates observed in clinical practice.

TROPIC Trial (JEVTANA 25 mg/m^2 compared to mitoxantrone)

The safety of JEVTANA in combination with prednisone was evaluated in 371 patients with metastatic castration-resistant prostate cancer treated in the randomized TROPIC trial, compared to mitoxantrone plus prednisone.

Deaths due to causes other than disease progression within 30 days of last study drug dose were reported in 18 (5%) JEVTANA-treated patients and 3 (<1%) mitoxantrone-treated patients. The most common fatal adverse reactions in JEVTANA-treated patients were infections (n=5) and renal failure (n=4). The majority (4 of 5 patients) of fatal infection-related adverse reactions occurred after a single dose of JEVTANA. Other fatal adverse reactions in JEVTANA-treated patients included ventricular fibrillation, cerebral hemorrhage, and dyspnea.

The most common (≥10%) grade 1–4 adverse reactions were anemia, leukopenia, neutropenia, thrombocytopenia, diarrhea, fatigue, nausea, vomiting, constipation, asthenia, abdominal pain, hematuria, back pain, anorexia, peripheral neuropathy, pyrexia, dyspnea, dysgeusia, cough, arthralgia, and alopecia.

The most common (≥5%) grade 3–4 adverse reactions in patients who received JEVTANA were neutropenia, leukopenia, anemia, febrile neutropenia, diarrhea, fatigue, and asthenia.

Treatment discontinuations due to adverse reactions occurred in 18% of patients who received JEVTANA and 8% of patients who received mitoxantrone. The most common adverse reactions leading to treatment discontinuation in the JEVTANA group were neutropenia and renal failure. Dose reductions were reported in 12% of JEVTANA-treated patients and 4% of mitoxantrone-treated patients. Dose delays were reported in 28% of JEVTANA-treated patients and 15% of mitoxantrone-treated patients.

Table 2: Adverse Reactions [Graded using NCI CTCAE version 3.] and Hematologic Abnormalities in ≥5% of Patients in TROPIC
Adverse Reactions | JEVTANA 25 mg/m^2 every 3 weeks with prednisone 10 mg daily n=371 |  | Mitoxantrone 12 mg/m^2 every 3 weeks with prednisone 10 mg daily n=371
Adverse Reactions | Grade 1–4 % | Grade 3–4 % | Grade 1–4 % | Grade 3–4 %
Blood and Lymphatic System Disorders
Anemia [Based on laboratory values, JEVTANA: n=369, mitoxantrone: n=370.] | 98 | 11 | 82 | 5
Leukopenia | 96 | 69 | 93 | 42
Neutropenia | 94 | 82 | 87 | 58
Thrombocytopenia | 48 | 4 | 43 | 2
Febrile Neutropenia | 7 | 7 | 1 | 1
Gastrointestinal Disorders
Diarrhea | 47 | 6 | 11 | <1
Nausea | 34 | 2 | 23 | <1
Vomiting | 22 | 2 | 10 | 0
Constipation | 20 | 1 | 15 | <1
Abdominal Pain [Includes abdominal discomfort, abdominal pain lower, abdominal pain upper, abdominal tenderness, and GI pain.] | 17 | 2 | 6 | 0
Dyspepsia [Includes gastroesophageal reflux disease and reflux gastritis.] | 10 | 0 | 2 | 0
General Disorders and Administration Site Conditions
Fatigue | 37 | 5 | 27 | 3
Asthenia | 20 | 5 | 12 | 2
Pyrexia | 12 | 1 | 6 | <1
Peripheral Edema | 9 | <1 | 9 | <1
Mucosal Inflammation | 6 | <1 | 3 | <1
Pain | 5 | 1 | 5 | 2
Renal and Urinary Tract Disorders
Hematuria | 17 | 2 | 4 | <1
Dysuria | 7 | 0 | 1 | 0
Musculoskeletal and Connective Tissue Disorders
Back Pain | 16 | 4 | 12 | 3
Arthralgia | 11 | 1 | 8 | 1
Muscle Spasms | 7 | 0 | 3 | 0
Metabolism and Nutrition Disorders
Anorexia | 16 | <1 | 11 | <1
Dehydration | 5 | 2 | 3 | <1
Nervous System Disorders
Peripheral Neuropathy [Includes peripheral motor neuropathy and peripheral sensory neuropathy.] | 13 | <1 | 3 | <1
Dysgeusia | 11 | 0 | 4 | 0
Dizziness | 8 | 0 | 6 | <1
Headache | 8 | 0 | 5 | 0
Respiratory, Thoracic and Mediastinal Disorders
Dyspnea | 12 | 1 | 4 | <1
Cough | 11 | 0 | 6 | 0
Skin and Subcutaneous Tissue Disorders
Alopecia | 10 | 0 | 5 | 0
Investigations
Weight Decreased | 9 | 0 | 8 | <1
Infections and Infestations
Urinary Tract Infection [Includes urinary tract infection enterococcal and urinary tract infection fungal.] | 8 | 2 | 3 | 1
Cardiac Disorders
Arrhythmia [Includes atrial fibrillation, atrial flutter, atrial tachycardia, atrioventricular block complete, bradycardia, palpitations, supraventricular tachycardia, tachyarrhythmia, and tachycardia.] | 5 | 1 | 2 | <1
Vascular Disorders
Hypotension | 5 | <1 | 2 | <1

PROSELICA Trial (comparison of two doses of JEVTANA)

In a noninferiority, multicenter, randomized, open-label study (PROSELICA), 1175 patients with metastatic castration-resistant prostate cancer, previously treated with a docetaxel-containing regimen, were treated with either JEVTANA 25 mg/m^2 (n=595) or the 20 mg/m^2 (n=580) dose.

Deaths within 30 days of last study drug dose were reported in 22 (3.8%) patients in the 20 mg/m^2 and 32 (5.4%) patients in the 25 mg/m^2 arm. The most common fatal adverse reactions in JEVTANA-treated patients were related to infections, and these occurred more commonly on the 25 mg/m^2 arm (n=15) than on the 20 mg/m^2 arm (n=8). Other fatal adverse reactions in JEVTANA-treated patients included cerebral hemorrhage, respiratory failure, paralytic ileus, diarrhea, acute pulmonary edema, disseminated intravascular coagulation, renal failure, sudden death, cardiac arrest, ischemic stroke, diverticular perforation, and cardiorenal syndrome.

Grade 1–4 adverse reactions occurring ≥5% more commonly in patients on the 25 mg/m^2 versus 20 mg/m^2 arms were leukopenia, neutropenia, thrombocytopenia, febrile neutropenia, decreased appetite, nausea, diarrhea, asthenia, and hematuria.

Grade 3–4 adverse reactions occurring ≥5% more commonly in patients on the 25 mg/m^2 versus 20 mg/m^2 arms were leukopenia, neutropenia, and febrile neutropenia.

Treatment discontinuations due to adverse reactions occurred in 17% of patients in the 20 mg/m^2 group and 20% of patients in the 25 mg/m^2 group. The most common adverse reactions leading to treatment discontinuation were fatigue and hematuria. The patients in the 20 mg/m^2 group received a median of 6 cycles (median duration of 18 weeks), while patients in the 25 mg/m^2 group received a median of 7 cycles (median duration of 21 weeks). In the 25 mg/m^2 group, 128 patients (22%) had a dose reduced from 25 to 20 mg/m^2, 19 patients (3%) had a dose reduced from 20 to 15 mg/m^2 and 1 patient (0.2%) had a dose reduced from 15 to 12 mg/m^2. In the 20 mg/m^2 group, 58 patients (10%) had a dose reduced from 20 to 15 mg/m^2, and 9 patients (2%) had a dose reduced from 15 to 12 mg/m^2.

Table 3: Adverse Reactions [Grade from NCI CTCAE version 4.03.] and Hematologic Abnormalities in ≥5% of Patients in PROSELICA
Adverse Reactions | JEVTANA 20 mg/m^2 every 3 weeks with prednisone 10 mg daily n=580 |  | JEVTANA 25 mg/m^2 every 3 weeks with prednisone 10 mg daily n=595
Adverse Reactions | Grade 1–4 % | Grade 3–4 % | Grade 1–4 % | Grade 3–4 %
Blood and Lymphatic System Disorders
Anemia [Based on laboratory values, JEVTANA 20 mg/m^2: n=577, JEVTANA 25 mg/m^2: n=590.] | 99.8 | 10 | 99.7 | 14
Leukopenia | 80 | 29 | 95 | 60
Neutropenia | 67 | 42 | 89 | 73
Thrombocytopenia | 35 | 3 | 43 | 4
Febrile Neutropenia | 2 | 2 | 9 | 9
Gastrointestinal Disorders
Diarrhea | 31 | 1 | 40 | 4
Nausea | 25 | 0.7 | 32 | 1
Constipation | 18 | 0.3 | 18 | 0.7
Vomiting | 15 | 1.2 | 18 | 1
Abdominal pain | 6 | 0.5 | 9 | 1
Stomatitis | 5 | 0 | 5 | 0.3
General Disorders and Administration Site Conditions
Fatigue | 25 | 3 | 27 | 4
Asthenia | 15 | 2 | 20 | 2
Edema peripheral | 7 | 0.2 | 9 | 0.2
Pyrexia | 5 | 0.2 | 6 | 0.2
Renal and Urinary Disorders
Hematuria | 14 | 2 | 21 | 4
Dysuria | 5 | 0.3 | 4 | 0
Metabolism and Nutrition Disorders
Decreased appetite | 13 | 0.7 | 19 | 1
Musculoskeletal and Connective Tissue Disorders
Back pain | 11 | 0.9 | 14 | 1
Bone pain | 8 | 2 | 8 | 2
Arthralgia | 8 | 0.5 | 7 | 0.8
Pain in extremity | 5 | 0.2 | 7 | 0.5
Nervous System Disorders
Dysgeusia | 7 | 0 | 11 | 0
Peripheral sensory neuropathy | 7 | 0 | 11 | 0.7
Dizziness | 4 | 0 | 5 | 0
Headache | 5 | 0.2 | 4 | 0.2
Infections and Infestations
Urinary tract infection [Includes urinary tract infection staphylococcal, urinary tract infection bacterial, urinary tract infection fungal, and urosepsis.] | 7 | 2 | 11 | 2
Neutropenic infection [Includes neutropenic sepsis.] | 3 | 2 | 7 | 6
Respiratory, Thoracic and Mediastinal Disorders
Dyspnea | 5 | 0.9 | 8 | 0.7
Cough | 6 | 0 | 6 | 0
Investigations
Weight decreased | 4 | 0.2 | 7 | 0
Skin and Subcutaneous Tissue Disorders
Alopecia | 3 | 0 | 6.1 | 0
Injury, Poisoning and Procedural Complications
Wrong technique in drug usage process | 0.3 | 0 | 5 | 0

CARD Trial (JEVTANA 25 mg/m^2 + primary prophylaxis with G-CSF)

The safety of JEVTANA 25 mg/m^2 in combination with prednisone/prednisolone and primary prophylaxis G-CSF was evaluated in a randomized, open-label study (CARD) in patients with metastatic castration-resistant prostate cancer who progressed after receiving prior docetaxel-containing regimens and abiraterone acetate or enzalutamide [see Clinical Studies 14.3]. This study compared JEVTANA 25 mg/m^2 in combination with prednisone/prednisolone and primary prophylaxis with G-CSF to either abiraterone acetate 1000 mg once daily plus prednisone/prednisolone 5 mg twice daily or enzalutamide 160 mg once daily. Among patients receiving JEVTANA, 35% remained on treatment at 6 months and 4.7% remained on treatment at 12 months.

Serious adverse reactions occurred in 39% of patients receiving JEVTANA. Serious adverse reactions in ≥3% of patients included neutropenia (6%), infections (4.8%), and diarrhea, fatigue, pneumonia, and spinal cord compression (3.2% each). Deaths due to causes other than disease progression were reported in 2.4% of JEVTANA treated patients. Fatal adverse reactions in JEVTANA-treated patients were septic shock, urinary tract infection (UTI), and aspiration (0.8% each).

Treatment discontinuations due to adverse drug reactions occurred in 20% of patients who received JEVTANA and 8% of patients who received abiraterone acetate plus prednisone/prednisolone or enzalutamide. The adverse reactions leading to treatment discontinuation in >1% of patients in JEVTANA arm were nervous system disorders, infections/infestations, and gastrointestinal disorders.

Dose interruptions (alone or in combination with dose reduction) due to an adverse reaction occurred in 31% of patients receiving JEVTANA. Dose reductions were reported in 18% of JEVTANA-treated patients. The most frequent adverse reactions leading to dose interruption of JEVTANA were fatigue (7%) and hypersensitivity reaction (3.2%); the most frequent adverse reaction leading to reduction of JEVTANA were neutropenia and peripheral neuropathy (3.9% each).

Table 4 summarizes the adverse reactions and laboratory hematologic abnormalities in patients in CARD.

The most common (≥10%) adverse reactions were fatigue, diarrhea, musculoskeletal pain, nausea, infections, peripheral neuropathy, hematuria, constipation, abdominal pain, decreased appetite, vomiting, dysgeusia, edema peripheral and lower urinary tract symptoms.

The most common (≥10%) hematologic abnormalities were anemia, lymphopenia, neutropenia and thrombocytopenia.

Table 4: Adverse Reactions [Grade from NCI CTC version 4.0.] and Hematologic Abnormalities in ≥5% of Patients in CARD Trial
Adverse Reactions | JEVTANA 25 mg/m^2 + prednisone/prednisolone + G-CSF |  | Abiraterone + prednisone/prednisolone or Enzalutamide
Adverse Reactions | (N=126) |  | (N=124)
Adverse Reactions | Grade 1–4 % | Grade 3–4 % | Grade 1–4 % | Grade 3–4 %
Blood and Lymphatic System Disorders
Anemia [Based on laboratory values - % calculated using the number of patients with at least one event(n) over the number of patients assessed for each parameter during the on-treatment period.] | 99 | 8 | 95 | 4.8
Lymphopenia | 72 | 27 | 55 | 17
Neutropenia | 66 | 45 | 7 | 3.2
Thrombocytopenia | 41 | 3.2 | 16 | 1.6
General Disorders and Administration Site Conditions
Fatigue [includes asthenia, fatigue, lethargy, malaise.] | 53 | 4 | 36 | 2.4
Edema peripheral [includes lymphoedema, edema peripheral, peripheral swelling.] | 11 | 0.8 | 10 | 1.6
Pyrexia | 6 | 0 | 7 | 0
Pain | 6 | 0 | 6 | 0.8
Gastrointestinal Disorders
Diarrhea [includes colitis, diarrhea, diarrhea hemorrhagic, gastroenteritis.] | 40 | 4.8 | 6 | 0
Nausea | 23 | 0 | 23 | 0.8
Constipation | 15 | 0 | 11 | 0
Abdominal pain [includes abdominal pain, abdominal pain lower, abdominal pain upper, flank pain, gastrointestinal pain.] | 14 | 1.6 | 6 | 0.8
Vomiting | 13 | 0 | 12 | 1.6
Stomatitis | 8 | 0 | 1.6 | 0
Dyspepsia | 4.8 | 0 | 2.4 | 0
Musculoskeletal and Connective Tissue Disorders
Musculoskeletal pain [includes arthralgia, back pain, bone pain, musculoskeletal chest pain, musculoskeletal discomfort, musculoskeletal pain, myalgia, neck pain, noncardiac chest pain.] | 27 | 1.6 | 40 | 6
Pain in extremity | 4.8 | 0 | 11 | 2.4
Bone fracture [includes femoral neck fracture, pathological fracture, rib fracture, spinal compression fracture, sternal fracture, thoracic vertebral fracture.] | 3.2 | 1.6 | 8 | 2.4
Infections and Infestations
Infections [includes bacteremia, bacteriuria, cellulitis, device related sepsis, Enterobacter sepsis, erysipelas, furuncle, influenza, influenza like illness, localized infection, oral fungal infection, perineal cellulitis, pulmonary sepsis, pyelocaliectasis, pyelonephritis, pyelonephritis acute, respiratory tract infection, respiratory tract infection viral, sepsis, septic shock, subcutaneous abscess, upper respiratory tract infection, ureteritis, urinary tract infection, urinary tract infection bacterial, urosepsis, viral infection.] | 19 | 4 | 14 | 6
Nervous System Disorders
Peripheral neuropathy [includes neuropathy peripheral, paresthesia, peripheral motor neuropathy, peripheral sensorimotor neuropathy, peripheral sensory neuropathy.] | 18 | 1.6 | 4.8 | 0
Dysgeusia | 11 | 0 | 4 | 0
Polyneuropathy | 6 | 1.6 | 0 | 0
Dizziness | 0.8 | 0 | 4.8 | 0
Renal and Urinary Disorders
Hematuria [includes hematuria, cystitis hemorrhagic.] | 16 | 0.8 | 6 | 1.6
Lower urinary tract symptoms [include lower urinary tract symptoms, micturition urgency, nocturia, pollakiuria, urinary incontinence, urinary retention, dysuria.] | 10 | 0 | 9 | 0
Acute kidney injury [includes acute kidney injury, blood creatinine increased, renal failure, renal impairment.] | 5 | 2.4 | 10 | 4
Metabolism and Nutrition Disorders
Decreased appetite | 14 | 0.8 | 15 | 2.4
Hypokalemia | 3.2 | 0 | 6 | 0
Neoplasms Benign, Malignant and Unspecified (incl cysts and polyps)
Cancer pain | 8 | 1.6 | 9 | 2.4
Cardiac disorders [includes aortic valve incompetence, aortic valve stenosis, atrial fibrillation, atrial flutter, atrioventricular block complete, atrioventricular block second degree, bradycardia, sinus bradycardia, tachycardia, cardiac failure, acute coronary syndrome, angina pectoris.] | 6 | 0.8 | 6 | 3.2
Respiratory, Thoracic and Mediastinal Disorders
Pneumonia [includes lower respiratory tract infection, lung infection, lung infiltration, pneumonia.] | 6 | 1.6 | 3.2 | 0.8
Dyspnea | 6 | 0 | 2.4 | 0
Skin and Subcutaneous Tissue Disorders
Alopecia | 6 | 0 | 0 | 0
Injury, Poisoning and Procedural Complications
Fall | 4.8 | 0 | 0 | 0
Vascular Disorders
Hypertension [includes hypertension, hypertensive crisis.] | 4 | 2.4 | 8 | 2.4
Investigations
Weight decreased | 4 | 0 | 6 | 0
Psychiatric Disorders
Insomnia | 3.2 | 0 | 4.8 | 0

Clinically relevant ≥ Grade 3 adverse reactions in <5% of patients who received JEVTANA in combination with prednisone and primary prophylaxis G-CSF: febrile neutropenia (3.2%), pulmonary embolism (1.6%), and neutropenic infection (0.8%).

Hematuria

In study TROPIC, adverse reactions of hematuria, including those requiring medical intervention, were more common in JEVTANA-treated patients. The incidence of grade ≥2 hematuria was 6% in JEVTANA-treated patients and 2% in mitoxantrone-treated patients. Other factors associated with hematuria were well-balanced between arms and do not account for the increased rate of hematuria on the JEVTANA arm.

In study PROSELICA, hematuria of all grades was observed in 18% of patients overall.

In CARD, hematuria of all grades was observed in 16% of patients receiving JEVTANA.

Hepatic Laboratory Abnormalities

The incidences of grade 3–4 increased AST, increased ALT, and increased bilirubin were each ≤1%.

6.2 Postmarketing Experience

The following adverse reactions have been identified from clinical trials and/or postmarketing surveillance. Because they are reported from a population of unknown size, precise estimates of frequency cannot be made.

Gastrointestinal: Gastritis, intestinal obstruction.

Respiratory: Interstitial pneumonia/pneumonitis, interstitial lung disease and acute respiratory distress syndrome.

Renal and urinary disorders: Radiation recall hemorrhagic cystitis.

7 DRUG INTERACTIONS

7.1 CYP3A Inhibitors

Cabazitaxel is primarily metabolized through CYP3A [see Clinical Pharmacology (12.3)]. Strong CYP3A inhibitors (e.g., ketoconazole, itraconazole, clarithromycin, atazanavir, indinavir, nefazodone, nelfinavir, ritonavir, saquinavir, telithromycin, voriconazole) may increase plasma concentrations of cabazitaxel. Avoid the coadministration of JEVTANA with strong CYP3A inhibitors. If patients require coadministration of a strong CYP3A inhibitor, consider a 25% JEVTANA dose reduction [see Dosage and Administration (2.4) and Clinical Pharmacology (12.3)].

8 USE IN SPECIFIC POPULATIONS

8.1 Pregnancy

Risk Summary

The safety and efficacy of JEVTANA have not been established in females. There are no human data on the use of JEVTANA in pregnant women to inform the drug-associated risk. In animal reproduction studies, intravenous administration of cabazitaxel in pregnant rats during organogenesis caused embryonic and fetal death at doses lower than the maximum recommended human dose [see Data].

Data

Animal data

In an early embryonic developmental toxicity study in rats, cabazitaxel was administered intravenously for 15 days prior to mating through day 6 of pregnancy, which resulted in an increase in pre-implantation loss at 0.2 mg/kg/day and an increase in early resorptions at ≥0.1 mg/kg/day (approximately 0.06 and 0.02 times the Cmax in patients at the recommended human dose, respectively).

In an embryo-fetal developmental toxicity study in rats, cabazitaxel caused maternal and embryo-fetal toxicity consisting of increased postimplantation loss, embryolethality, and fetal deaths when administered intravenously at a dose of 0.16 mg/kg/day (approximately 0.06 times the Cmax in patients at the recommended human dose). Decreased mean fetal birthweight associated with delays in skeletal ossification was observed at doses ≥0.08 mg/kg. Cabazitaxel crossed the placenta barrier within 24 hours of a single intravenous administration of 0.08 mg/kg to pregnant rats at gestational day 17. A dose of 0.08 mg/kg in rats resulted in a Cmax approximately 0.02 times that observed in patients at the recommended human dose. Administration of cabazitaxel did not result in fetal abnormalities in rats or rabbits at exposure levels significantly lower than the expected human exposures.

8.2 Lactation

Risk Summary

The safety and efficacy of JEVTANA have not been established in females. There is no information available on the presence of cabazitaxel in human milk, the effects of the drug on the breastfed infant, or the effects of the drug on milk production. Cabazitaxel or cabazitaxel metabolites are excreted in maternal milk of lactating rats [see Data].

Data

Animal data

In a milk excretion study, radioactivity related to cabazitaxel was detected in the stomachs of nursing pups within 2 hours of a single intravenous administration of cabazitaxel to lactating rats at a dose of 0.08 mg/kg (approximately 0.02 times the Cmax in patients at the recommended human dose). This was detectable 24 hours post dose. Approximately 1.5% of the dose delivered to the mother was calculated to be delivered in the maternal milk.

8.3 Females and Males of Reproductive Potential

Contraception

Males

Based on findings in animal reproduction studies, advise male patients with female partners of reproductive potential to use effective contraception during treatment and for 4 months after the last dose of JEVTANA [see Use in Specific Populations (8.1)].

Infertility

Males

Based on animal toxicology studies, JEVTANA may impair human fertility in males of reproductive potential [see Nonclinical Toxicology (13.1)].

8.4 Pediatric Use

The safety and effectiveness of JEVTANA in pediatric patients have not been established.

JEVTANA was evaluated in 39 pediatric patients (ages 3 to 18 years) receiving prophylactic G-CSF. The maximum tolerated dose (MTD) was 30 mg/m^2 intravenously over 1 hour on Day 1 of a 21 day cycle in pediatric patients with solid tumors based on the dose-limiting toxicity (DLT) of febrile neutropenia. No objective responses were observed in 11 patients with refractory high grade glioma (HGG) or diffuse intrinsic pontine glioma (DIPG). One patient had a partial response among the 9 patients with ependymoma.

Infusion related/hypersensitivity reactions were seen in 10 patients (26%). Three patients experienced serious adverse events of anaphylactic reaction. The incidence of infusion related/hypersensitivity reactions decreased with steroid premedication. The most frequent treatment-emergent adverse events were similar to those reported in adults.

Based on the population pharmacokinetics analysis conducted with data from 31 pediatric patients with cancer (ages 3 to 18 years), the clearances by body surface area were comparable to those in adults.

8.5 Geriatric Use

In the TROPIC study, of the 371 patients with prostate cancer treated with JEVTANA every three weeks plus prednisone, 240 patients (64.7%) were 65 years of age and over, while 70 patients (18.9%) were 75 years of age and over. No overall differences in effectiveness were observed between patients ≥65 years of age and younger patients. Elderly patients (≥65 years of age) may be more likely to experience certain adverse reactions. The incidence of death due to causes other than disease progression within 30 days of the last cabazitaxel dose were higher in patients who were 65 years of age or greater compared to younger patients [see Warnings and Precautions (5.2)]. The incidence of grade 3–4 neutropenia and febrile neutropenia were higher in patients who were 65 years of age or greater compared to younger patients. The following grade 1–4 adverse reactions were reported at rates ≥5% higher in patients 65 years of age or older compared to younger patients: fatigue (40% vs 30%), neutropenia (97% vs 89%), asthenia (24% vs 15%), pyrexia (15% vs 8%), dizziness (10% vs 5%), urinary tract infection (10% vs 3%), and dehydration (7% vs 2%), respectively.

In the PROSELICA study, the grade 1–4 adverse reactions reported at rates of at least 5% higher in patients 65 years of age or older compared to younger patients were diarrhea (43% vs 33%), fatigue (30% vs 19%), asthenia (22% vs 13%), constipation (20% vs 13%), clinical neutropenia (13% vs 6%), febrile neutropenia (11% vs 5%), and dyspnea (10% vs 3%).

In the CARD study, the grade 1–4 adverse reactions reported at rates of at least 5% higher in patients 65 years of age or older compared to younger patients were decreased appetite (16% vs 7%), hypertension (5% vs 0), constipation (18% vs 7%), paresthesia (6% vs 0), stomatitis (10% vs 3%), musculoskeletal pain (5% vs 0), fatigue (31% vs 23%), asthenia (30% vs 19%), and edema peripheral (11% vs 0).

Based on a population pharmacokinetic analysis, no significant difference was observed in the pharmacokinetics of cabazitaxel between patients <65 years (n=100) and older (n=70).

8.6 Renal Impairment

No dose adjustment is necessary in patients with renal impairment not requiring hemodialysis. Patients presenting with end-stage renal disease (creatinine clearance CLCR <15 mL/min/1.73 m^2), should be monitored carefully during treatment [see Clinical Pharmacology (12.3)].

8.7 Hepatic Impairment

Cabazitaxel is extensively metabolized in the liver. Patients with mild hepatic impairment (total bilirubin >1 to ≤1.5 × ULN or AST >1.5 × ULN) should have JEVTANA dose of 20 mg/m^2. Administration of cabazitaxel to patients with mild hepatic impairment should be undertaken with caution and close monitoring of safety [see Clinical Pharmacology (12.3)]. The maximum tolerated dose in patients with moderate hepatic impairment (total bilirubin >1.5 to ≤3.0 × ULN and AST = any) was 15 mg/m^2, however, the efficacy at this dose level was unknown. JEVTANA is contraindicated in patients with severe hepatic impairment (total bilirubin >3 × ULN) [see Contraindications (4)].

10 OVERDOSAGE

There is no known antidote for JEVTANA overdose. Overdose has resulted from improper preparation [see Dosage and Administration (2.5)]. Read the entire section Dosage and Administration (2) carefully before mixing or diluting. Complications of overdose include exacerbation of adverse reactions such as bone marrow suppression and gastrointestinal disorders. Overdose has led to fatal outcome.

In case of overdose, the patient should be kept in a specialized unit where vital signs, chemistry and particular functions can be closely monitored. Patients should receive therapeutic G-CSF as soon as possible after discovery of overdose. Other appropriate symptomatic measures should be taken, as needed.

11 DESCRIPTION

JEVTANA (cabazitaxel) injection is an antineoplastic agent belonging to the taxane class that is for intravenous use. It is prepared by semi-synthesis with a precursor extracted from yew needles.

The chemical name of cabazitaxel is (2α,5β,7β,10β,13α)-4-acetoxy-13-({(2R,3S)-3-[(tertbutoxycarbonyl) amino]-2-hydroxy-3-phenylpropanoyl}oxy)-1-hydroxy-7,10-dimethoxy-9-oxo-5,20-epoxytax-11-en-2-yl benzoate – propan-2-one (1:1).

Cabazitaxel has the following structural formula:

Cabazitaxel is a white to almost-white powder with a molecular formula of C45H57NO14C3H6O and a molecular weight of 894.01 (for the acetone solvate) / 835.93 (for the solvent free). It is lipophilic, practically insoluble in water and soluble in alcohol.

JEVTANA (cabazitaxel) injection 60 mg/1.5 mL is a sterile, non-pyrogenic, clear yellow to brownish-yellow viscous solution and is available in single-dose vials containing 60 mg cabazitaxel (anhydrous and solvent free) and 1.56 g polysorbate 80 (citric acid monohydrate is used to adjust the pH of the polysorbate 80 between 3.3 to 3.8).

Each mL contains 40 mg cabazitaxel (anhydrous) and 1.04 g polysorbate 80.

DILUENT for JEVTANA is a clear, colorless, sterile, and non-pyrogenic solution containing 13% (w/w) ethanol in water for injection, approximately 5.7 mL.

JEVTANA requires two dilutions prior to intravenous infusion. JEVTANA injection should be diluted only with the supplied DILUENT for JEVTANA, followed by dilution in either 0.9% sodium chloride solution or 5% dextrose solution.

12 CLINICAL PHARMACOLOGY

12.1 Mechanism of Action

Cabazitaxel is a microtubule inhibitor. Cabazitaxel binds to tubulin and promotes its assembly into microtubules while simultaneously inhibiting disassembly. This leads to the stabilization of microtubules, which results in the inhibition of mitotic and interphase cellular functions.

12.2 Pharmacodynamics

Cardiac Electrophysiology

The effect of cabazitaxel following a single dose of 25 mg/m^2 administered by intravenous infusion on QTc interval was evaluated in 94 patients with solid tumors. No large changes in the mean QT interval (i.e., >20 ms) from baseline based on Fridericia correction method were detected. However, a small increase in the mean QTc interval (i.e., <10 ms) cannot be excluded due to study design limitations.

12.3 Pharmacokinetics

A population pharmacokinetic analysis was conducted in 170 patients with solid tumors at doses ranging from 10 to 30 mg/m^2 weekly or every three weeks.

Absorption

Based on the population pharmacokinetic analysis, after an intravenous dose of cabazitaxel 25 mg/m^2 every three weeks, the mean Cmax in patients with metastatic prostate cancer was 226 ng/mL (CV 107%) and was reached at the end of the one-hour infusion (Tmax). The mean AUC in patients with metastatic prostate cancer was 991 ng∙h/mL (CV 34%).

No major deviation from the dose proportionality was observed from 10 to 30 mg/m^2 in patients with advanced solid tumors.

Distribution

The volume of distribution (Vss) was 4,864 L (2,643 L/m^2 for a patient with a median BSA of 1.84 m^2) at steady state.

In vitro, the binding of cabazitaxel to human serum proteins was 89% to 92% and was not saturable up to 50,000 ng/mL, which covers the maximum concentration observed in clinical trials. Cabazitaxel is mainly bound to human serum albumin (82%) and lipoproteins (88% for HDL, 70% for LDL, and 56% for VLDL). The in vitro blood-to-plasma concentration ratio in human blood ranged from 0.90 to 0.99, indicating that cabazitaxel was equally distributed between blood and plasma.

Metabolism

Cabazitaxel is extensively metabolized in the liver (>95%), mainly by the CYP3A4/5 isoenzyme (80% to 90%), and to a lesser extent by CYP2C8. Cabazitaxel is the main circulating moiety in human plasma. Seven metabolites were detected in plasma (including the 3 active metabolites issued from O-demethylation), with the main one accounting for 5% of cabazitaxel exposure. Around 20 metabolites of cabazitaxel are excreted into human urine and feces.

Elimination

After a one-hour intravenous infusion [^14C]-cabazitaxel 25 mg/m^2, approximately 80% of the administered dose was eliminated within 2 weeks. Cabazitaxel is mainly excreted in the feces as numerous metabolites (76% of the dose); while renal excretion of cabazitaxel and metabolites account for 3.7% of the dose (2.3% as unchanged drug in urine).

Based on the population pharmacokinetic analysis, cabazitaxel has a plasma clearance of 48.5 L/h (CV 39%; 26.4 L/h/m^2 for a patient with a median BSA of 1.84 m^2) in patients with metastatic prostate cancer. Following a one-hour intravenous infusion, plasma concentrations of cabazitaxel can be described by a three-compartment pharmacokinetic model with α-, β-, and γ- half-lives of 4 minutes, 2 hours, and 95 hours, respectively.

Renal Impairment

Cabazitaxel is minimally excreted via the kidney. A population pharmacokinetic analysis carried out in 170 patients including 14 patients with moderate renal impairment (30 mL/min ≤CLCR <50 mL/min) and 59 patients with mild renal impairment (50 mL/min ≤CLCR <80 mL/min) showed that mild to moderate renal impairment did not have meaningful effects on the pharmacokinetics of cabazitaxel. This was confirmed by a dedicated comparative pharmacokinetic study in patients with solid tumors with normal renal function (n=8, CLCR >80 mL/min/1.73 m^2), or moderate (n=8, 30 mL/min/1.73 m^2 ≤CLCR <50 mL/min/1.73 m^2) and severe (n=9, CLCR <30 mL/min/1.73 m^2) renal impairment, who received several cycles of cabazitaxel in single IV infusion up to 25 mg/m^2. Limited pharmacokinetic data were available in patients with end-stage renal disease (n=2, CLCR <15 mL/min/1.73 m^2).

Hepatic Impairment

Cabazitaxel is extensively metabolized in the liver.

A dedicated study in 43 cancer patients with hepatic impairment showed no influence of mild (total bilirubin >1 to ≤1.5 × ULN or AST >1.5 × ULN) or moderate (total bilirubin >1.5 to ≤3.0 × ULN) hepatic impairment on cabazitaxel pharmacokinetics. The maximum tolerated dose (MTD) of cabazitaxel was 20 and 15 mg/m^2, respectively.

In 3 patients with severe hepatic impairment (total bilirubin >3 × ULN), a 39% decrease in clearance was observed when compared to patients with mild hepatic impairment (ratio=0.61, 90% CI: 0.36–1.05), indicating some effect of severe hepatic impairment on cabazitaxel pharmacokinetics. The MTD of cabazitaxel in patients with severe hepatic impairment was not established. Based on safety and tolerability data, cabazitaxel dose should be maintained at 20 mg/m^2 in patients with mild hepatic impairment and reduced to 15 mg/m^2 in patients with moderate hepatic impairment [see Warnings and Precautions (5.8) and Use in Specific Populations (8.7)]. Cabazitaxel is contraindicated in patients with severe hepatic impairment [see Contraindications (4) and Use in Specific Populations (8.7)].

Drug Interactions

A drug interaction study of JEVTANA in 23 patients with advanced cancers has shown that repeated administration of ketoconazole (400 mg orally once daily), a strong CYP3A inhibitor, increased the exposure to cabazitaxel (5 mg/m^2 intravenous) by 25%.

A drug interaction study of JEVTANA in 13 patients with advanced cancers has shown that repeated administration of aprepitant (125 or 80 mg once daily), a moderate CYP3A inhibitor, did not modify the exposure to cabazitaxel (15 mg/m^2 intravenous).

A drug interaction study of JEVTANA in 21 patients with advanced cancers has shown that repeated administration of rifampin (600 mg once daily), a strong CYP3A inducer, decreased the exposure to cabazitaxel (15 mg/m^2 intravenous) by 17%.

A drug interaction study of JEVTANA in 11 patients with advanced cancers has shown that cabazitaxel (25 mg/m^2 administered as a single 1-hour infusion) did not modify the exposure to midazolam, a probe substrate of CYP3A.

Prednisone or prednisolone administered at 10 mg daily did not affect the pharmacokinetics of cabazitaxel.

Based on in vitro studies, the potential for cabazitaxel to inhibit drugs that are substrates of other CYP isoenzymes (1A2, -2B6, -2C9, -2C8, -2C19, -2E1, -2D6, and CYP3A4/5) is low. In addition, cabazitaxel did not induce CYP isozymes (-1A, -2C9 and -3A) in vitro.

In vitro, cabazitaxel did not inhibit the multidrug-resistance protein 1 (MRP1), 2 (MRP2) or organic cation transporter (OCT1). In vitro, cabazitaxel inhibited P-gp, BRCP, and organic anion transporting polypeptides (OATP1B1, OATP1B3). However, the in vivo risk of cabazitaxel inhibiting MRPs, OCT1, P-gp, BCRP, OATP1B1 or OATP1B3 is low at the dose of 25 mg/m^2.

In vitro, cabazitaxel is a substrate of P-gp, but not a substrate of MRP1, MRP2, BCRP, OCT1, OATP1B1 or OATP1B3.

13 NONCLINICAL TOXICOLOGY

13.1 Carcinogenesis, Mutagenesis, Impairment of Fertility

Long-term animal studies have not been performed to evaluate the carcinogenic potential of cabazitaxel.

Cabazitaxel was positive for genotoxicity by an aneugenic mechanism in the in vivo micronucleus test, inducing an increase of micronuclei in rats at doses ≥0.5 mg/kg. Cabazitaxel increased numerical aberrations with or without metabolic activation in an in vitro test in human lymphocytes though no induction of structural aberrations was observed. Cabazitaxel did not induce mutations in the bacterial reverse mutation (Ames) test. The positive in vivo genotoxicity findings are consistent with the pharmacological activity of the compound (inhibition of tubulin depolymerization).

In a fertility study performed in female rats at cabazitaxel doses of 0.05, 0.1, or 0.2 mg/kg/day there was no effect of administration of the drug on mating behavior or the ability to become pregnant. In repeat-dose toxicology studies in rats with intravenous cabazitaxel administration once every three weeks for up to 6 months, atrophy of the uterus was observed at the 5 mg/kg dose level (approximately the AUC in patients with cancer at the recommended human dose) along with necrosis of the corpora lutea at doses ≥1 mg/kg (approximately 0.2 times the AUC at the clinically recommended human dose).

In a fertility study in male rats, cabazitaxel did not affect mating performances or fertility at doses of 0.05, 0.1, or 0.2 mg/kg/day. In repeat-dose toxicology studies with intravenous cabazitaxel administration once every three weeks for up to 9 months, degeneration of seminal vesicle and seminiferous tubule atrophy in the testis were observed in rats at a dose of 1 mg/kg (approximately 0.2 times the AUC in patients at the recommended human dose), and minimal testicular degeneration (minimal epithelial single cell necrosis in epididymis) was observed in dogs treated at a dose of 0.5 mg/kg (approximately 0.1 times the AUC in patients at the recommended human dose).

14 CLINICAL STUDIES

14.1 TROPIC Trial (JEVTANA + prednisone compared to mitoxantrone)

The efficacy and safety of JEVTANA in combination with prednisone were evaluated in a randomized, open-label, international, multi-center study in patients with metastatic castration-resistant prostate cancer previously treated with a docetaxel-containing treatment regimen (TROPIC, NCT00417079).

A total of 755 patients were randomized to receive either JEVTANA 25 mg/m^2 intravenously every 3 weeks for a maximum of 10 cycles with prednisone 10 mg orally daily (n=378), or to receive mitoxantrone 12 mg/m^2 intravenously every 3 weeks for 10 cycles with prednisone 10 mg orally daily (n=377) for a maximum of 10 cycles.

This study included patients over 18 years of age with hormone-refractory metastatic prostate cancer either measurable by RECIST criteria or non-measurable disease with rising PSA levels or appearance of new lesions, and ECOG (Eastern Cooperative Oncology Group) performance status 0–2. Patients had to have neutrophils >1,500 cells/mm^3, platelets >100,000 cells/mm^3, hemoglobin >10 g/dL, creatinine <1.5 × upper limit of normal (ULN), total bilirubin <1 × ULN, AST <1.5 × ULN, and ALT <1.5 × ULN. Patients with a history of congestive heart failure, or myocardial infarction within the last 6 months, or patients with uncontrolled cardiac arrhythmias, angina pectoris, and/or hypertension were not included in the study.

Demographics, including age, race, and ECOG performance status (0–2) were balanced between the treatment arms. The median age was 68 years (range 46–92) and the racial distribution for all groups was 83.9% Caucasian, 6.9% Asian, 5.3% Black, and 4% Others in the JEVTANA group.

Efficacy results for the JEVTANA arm versus the control arm are summarized in Table 5 and Figure 1.

Table 5: Efficacy of JEVTANA in TROPIC in the Treatment of Patients with Metastatic Castration-Resistant Prostate Cancer (intent-to-treat analysis)
 | JEVTANA + Prednisone n=378 | Mitoxantrone + Prednisone n=377
Overall Survival
Number of deaths (%) | 234 (61.9%) | 279 (74.0%)
Median survival (month) (95% CI) | 15.1 (14.1–16.3) | 12.7 (11.6–13.7)
Hazard Ratio [Hazard ratio estimated using Cox model; a hazard ratio of less than 1 favors JEVTANA.] (95% CI) | 0.70 (0.59–0.83)
p-value | <0.0001

Figure 1: Kaplan-Meier Overall Survival Curves (TROPIC)

Investigator-assessed tumor response of 14.4% (95% CI: 9.6–19.3) was higher for patients in the JEVTANA arm compared to 4.4% (95% CI: 1.6–7.2) for patients in the mitoxantrone arm, p=0.0005.

14.2 PROSELICA Trial (comparison of two doses of JEVTANA)

The efficacy and safety of JEVTANA were evaluated in a noninferiority, multicenter, randomized, open-label study (PROSELICA, NCT01308580). A total of 1200 patients with metastatic castration-resistant prostate cancer, previously treated with a docetaxel-containing regimen were randomized to receive either JEVTANA 25 mg/m^2 (n=602) or 20 mg/m^2 (n=598) dose. Overall survival (OS) was the major efficacy outcome.

Demographics, including age, race, and ECOG performance status (0–2) were balanced between the treatment arms. The median age was 68 years (range 45–89) and the racial distribution for all groups was 87% Caucasian, 6.9% Asian, 2.3% Black, and 3.8% Others in the JEVTANA 20 mg/m^2 group. The median age was 69 years (range 45–88) and the racial distribution for all groups was 88.7% Caucasian, 6.6% Asian, 1.8% Black, and 2.8% Others in the JEVTANA 25 mg/m^2 group.

The study demonstrated noninferiority in overall survival (OS) of JEVTANA 20 mg/m^2 in comparison with JEVTANA 25 mg/m^2 in an intent-to-treat population (see Table 6 and Figure 2). Based on the per-protocol population, the estimated median OS was 15.1 months on JEVTANA 20 mg/m^2 and 15.9 months on JEVTANA 25 mg/m^2, the observed hazard ratio (HR) of OS was 1.042 (97.78% CI: 0.886, 1.224). Among the subgroup analyses intended for assessing the heterogeneity, no notable difference in OS was observed on the JEVTANA 25 mg/m^2 arm compared to the JEVTANA 20 mg/m^2 arm in subgroups based on the stratification factors of ECOG performance status score, measurability of disease, or region.

Table 6: Overall Survival in PROSELICA for JEVTANA 20 mg/m^2 versus JEVTANA 25 mg/m^2 (intent-to-treat analysis)
 | CBZ20+PRED n=598 | CBZ25+PRED n=602
Overall Survival
Number of deaths, n (%) | 497 (83.1%) | 501 (83.2%)
Median survival (95% CI) (months) | 13.4 (12.2 to 14.9) | 14.5 (13.5 to 15.3)
Hazard Ratio [Hazard ratio is estimated using a Cox Proportional Hazards regression model. A hazard ratio <1 indicates a lower risk of death for Cabazitaxel 20 mg/m^2 with respect to 25 mg/m^2.] (97.78% CI [Adjusted for interim OS analyses. The noninferiority margin is 1.214.]) | 1.024 (0.886, 1.184)
CBZ20=Cabazitaxel 20 mg/m^2, CBZ25=Cabazitaxel 25 mg/m^2, PRED=Prednisone/Prednisolone.
CI=confidence interval.

Figure 2: Kaplan-Meier Overall Survival Curves (intent-to-treat population) (PROSELICA)

14.3 CARD Trial (JEVTANA 25 mg/m^2 + prednisone/prednisolone + primary prophylaxis with G-CSF compared to abiraterone acetate + prednisone/prednisolone or enzalutamide)

The efficacy and safety of JEVTANA were evaluated in a multinational, randomized, active-controlled, open-label study (CARD: NCT02485691) in patients with metastatic castration resistant prostate cancer (mCRPC) previously treated with a docetaxel containing regimen and had progressed within 12 months of initiating either abiraterone or enzalutamide. A total of 255 patients were randomized to receive either JEVTANA 25 mg/m^2 every 3 week plus prednisone/prednisolone 10 mg daily (n=129), abiraterone 1000 mg once daily plus prednisone/prednisolone 5 mg twice daily or enzalutamide 160 mg once daily depending on prior therapy received (n=126). Primary prophylactic G-CSF was administered at each cycle for patients in the JEVTANA arm. This study included patients over 18 years of age with ECOG performance status 0–2. Patients had to have neutrophils >1,500 cells/mm^3, platelets >100,000 cells/mm^3, hemoglobin >10 g/dL, creatinine <1.5 × upper limit of normal (ULN), total bilirubin <1 × ULN, AST <1.5 × ULN, and ALT <1.5 × ULN. Patients with a history of congestive heart failure, or myocardial infarction within the last 6 months, or patients with uncontrolled cardiac arrhythmias, angina pectoris, and/or hypertension were not included in the study. Randomization was stratified by ECOG performance status (0 or 1 vs 2), time from abiraterone acetate or enzalutamide to disease progression, and receipt of abiraterone acetate or enzalutamide before or after docetaxel containing regimen.

The major efficacy outcome measure was radiographic progression free-survival (rPFS) as defined by Prostate Cancer Working Group-2 (PCWG2) assessed by study investigators. Other efficacy outcome measures included overall survival and objective response rate.

Demographics and baseline disease characteristics were balanced between treatment arms. The overall median age was 70 years (range 45 to 88), 95% of patients had an ECOG PS of 0 to 1 and median Gleason score was 8. A majority of the patients (61%) had their prior treatment with abiraterone acetate or enzalutamide after docetaxel. There were 36% of patients on the cabazitaxel arm with visceral disease (liver 8%, lung 8%, other 20%) and 57% with bone-only disease. Race and ethnicity data were not collected. Approximately 92% of the patients on the cabazitaxel arm received primary prophylaxis with G-CSF therapy during the first 3 cycles and, overall, 90% of the patients on the cabazitaxel arm received primary prophylaxis with G-CSF therapy at each cycle.

Efficacy results from the CARD trial are summarized in Table 7 and Figure 3.

Table 7: Efficacy of JEVTANA in CARD Trial in the Treatment of Patients with Metastatic Castration-Resistant Prostate Cancer (intent-to-treat analysis)
 | JEVTANA + prednisone/prednisolone + G-CSF n=129 | Abiraterone + prednisone/prednisolone or Enzalutamide n=126
Radiographic Progression Free Survival (rPFS)
Number of events (%) [Investigator assessed.] | 95 (73.6%) | 101 (80.2%)
Median rPFS (months) (95% CI) | 8.0 (5.7 to 9.2) | 3.7 (2.8 to 5.1)
Hazard Ratio (95% CI) | 0.54 (0.40 to 0.73)
p-value [Stratified log-rank test, significance threshold = 0.05.] | <0.0001
Overall Survival (OS) [Overall survival was statistically significant.]
Median OS [95% CI] (months) | 13.6 [11.5; 17.5] | 11.0 [9.2; 12.9]
Hazard Ratio (95% CI) | 0.64 [0.46; 0.89]
p-value | 0.0078

Figure 3: Kaplan-Meier of Radiographic PFS (ITT Population)

In terms of therapy sequence prior to randomization, rPFS was consistent across the subgroups of patients who received abiraterone acetate/enzalutamide prior to docetaxel (HR=0.61, 95% CI: 0.39, 0.96) and those who received abiraterone acetate/enzalutamide after docetaxel (HR=0.48, 95% CI: 0.32, 0.70).

Objective tumor response rate assessed by study investigators was 36.5% (95% CI: 26.6 to 48.4) for JEVTANA arm versus 11.5% (95% CI: 2.9 to 20.2) for abiraterone acetate plus prednisone/prednisolone or enzalutamide arm, p=0.004.

15 REFERENCES

1. OSHA Hazardous Drugs. OSHA. http://www.osha.gov/SLTC/hazardousdrugs/index.html

16 HOW SUPPLIED/STORAGE AND HANDLING

16.1 How Supplied

JEVTANA is supplied as a kit, NDC 0024-5824-11, that contains the following:

- One single-dose vial of JEVTANA (cabazitaxel) injection: a clear yellow to brownish-yellow viscous solution of 60 mg/1.5 mL in a clear glass vial with a grey rubber closure, aluminum cap, and light green plastic flip-off cap (JEVTANA vial NDC 0024-5823-15).
- One single-dose vial of Diluent for JEVTANA: a clear colorless solution of 13% (w/w) ethanol in water for injection in a clear glass vial with a grey rubber closure, gold-color aluminum cap, and colorless plastic flip-off cap (diluent vial NDC 0024-5822-01).

16.2 Storage

JEVTANA injection and Diluent for JEVTANA:

Store at 25°C (77°F); excursions permitted between 15°C–30°C (59°F–86°F).

Do not refrigerate.

16.3 Handling and Disposal

JEVTANA is a hazardous anticancer drug. Follow applicable special handling and disposable procedures [see References (15)].

17 PATIENT COUNSELING INFORMATION

Advise the patient to read the FDA-approved patient labeling (Patient Information).

Hypersensitivity Reactions

Educate patients about the risk of potential hypersensitivity associated with JEVTANA. Confirm patients do not have a history of severe hypersensitivity reactions to cabazitaxel or to other drugs formulated with polysorbate 80. Instruct patients to immediately report signs of a hypersensitivity reaction [see Contraindications (4) and Warnings and Precautions (5.3)].

Bone Marrow Suppression

Inform patients that JEVTANA decreases blood count such as white blood cells, platelets and red blood cells. Thus, it is important that periodic assessment of their blood count be performed to detect the development of neutropenia, thrombocytopenia, anemia, and/or pancytopenia [see Contraindications (4) and Warnings and Precautions (5.1)]. Instruct patients to monitor their temperature frequently and immediately report any occurrence of fever to their healthcare provider.

Increased Toxicities in Elderly Patients

Inform elderly patients that certain side effects may be more frequent or severe [see Warnings and Precautions (5.2) and Use in Specific Populations (8.5)].

Importance of Prednisone

Explain that it is important to take the oral prednisone as prescribed. Instruct patients to report if they were not compliant with oral corticosteroid regimen [see Dosage and Administration (2.1)].

Infections, Dehydration, Renal Failure

Explain to patients that severe and fatal infections, dehydration, and renal failure have been associated with cabazitaxel exposure. Patients should immediately report fever, significant vomiting or diarrhea, decreased urinary output, and hematuria to their healthcare provider [see Warnings and Precautions (5.1, 5.4, 5.5)].

Urinary Disorders Including Cystitis

Inform patients that hematuria may occur during treatment with JEVTANA. Inform patients that previously received pelvic radiation that cystitis and radiation cystitis may occur during treatment with JEVTANA. Advise patients to report any occurrence of hematuria, or any signs and symptoms of cystitis or radiation cystitis, to their healthcare provider [see Warnings and Precautions (5.6)].

Respiratory Disorders

Explain to patients that severe and fatal interstitial pneumonia/pneumonitis, interstitial lung disease and acute respiratory distress syndrome have occurred with JEVTANA. Instruct patients to immediately report new or worsening pulmonary symptoms to their healthcare provider [see Warnings and Precautions (5.7)].

Drug Interactions

Inform patients about the risk of drug interactions and the importance of providing a list of prescription and non-prescription drugs to their healthcare provider [see Drug Interactions (7.1)].

Embryo-Fetal Toxicity

Advise male patients with female partners of reproductive potential to use effective contraception during treatment and for 4 months after the last dose of JEVTANA [see Use in Specific Populations (8.3)].

Infertility

Advise male patients that JEVTANA may impair fertility [see Use in Specific Populations (8.3)].

Manufactured by:
sanofi-aventis U.S. LLC
Morristown, NJ 07960
A SANOFI COMPANY

JEVTANA is a registered trademark of sanofi-aventis
©2025 sanofi-aventis U.S. LLC

Patient Information
JEVTANA® (JEV-ta-na)
(cabazitaxel)
injection

What is the most important information I should know about JEVTANA?
JEVTANA may cause serious side effects including:

- Low white blood cell count. Low white blood cell counts are common during treatment with JEVTANA and can cause serious infections that may lead to death. Men who are 65 years or older may be more likely to have these problems. Your healthcare provider:
  - will do blood tests regularly to check your white blood cell counts during your treatment with JEVTANA.
  - may lower your dose of JEVTANA, change how often you receive it, or stop JEVTANA until your healthcare provider decides that you have enough white blood cells.
  - may prescribe a medicine for you called G-CSF to help prevent complications if your white blood cell count is too low.
  Tell your healthcare provider right away if you have any of these symptoms of infection during treatment with JEVTANA:
  - fever. Take your temperature often during treatment with JEVTANA.
  - cough
  - burning on urination
  - muscle aches
  Also, tell your healthcare provider if you have any diarrhea during the time that your white blood cell count is low. Your healthcare provider may prescribe treatment for you as needed.
- Severe allergic reactions. Severe allergic reactions can happen within a few minutes after your infusion of JEVTANA starts, especially during the first and second infusions. Your healthcare provider should prescribe medicines before each infusion to help prevent severe allergic reactions.
  Tell your healthcare provider or nurse right away if you have any of these symptoms of a severe allergic reaction during or soon after an infusion of JEVTANA:

- rash or itching
- feeling dizzy or faint
- chest or throat tightness

- skin redness
- breathing problems
- swelling of your face

- Severe stomach and intestine (gastrointestinal) problems.
  - JEVTANA can cause severe vomiting and diarrhea, which may lead to death. Severe vomiting and diarrhea with JEVTANA can lead to loss of too much body fluid (dehydration), or too much of your body salts (electrolytes). Death has happened from having severe diarrhea and losing too much body fluid or body salts with JEVTANA. You may need to go to a hospital for treatment. Your healthcare provider will prescribe medicines to prevent or treat vomiting and diarrhea, as needed, with JEVTANA.
    Tell your healthcare provider right away if you develop vomiting or diarrhea or if your symptoms get worse or do not get better.
  - JEVTANA can cause a leak in the stomach or intestine, intestinal blockage, infection, and bleeding in the stomach or intestine, which may lead to death.
    Tell your healthcare provider if you develop any of these symptoms:
    - severe stomach-area (abdomen) pain
    - constipation
    - fever
    - blood in your stool, or changes in the color of your stool
- Kidney failure. Kidney failure may happen with JEVTANA, because of severe infection, loss of too much body fluid (dehydration), and other reasons, which may lead to death. Your healthcare provider will check you for this problem and treat you if needed.
  Tell your healthcare provider if you develop these signs or symptoms:
  - swelling of your face or body
  - decrease in the amount of urine that your body makes each day
  - blood in your urine
- Inflammation of the bladder and blood in the urine. Blood in the urine is common with JEVTANA, but it can also sometimes be severe. Some people who have had pelvic radiation in the past may develop inflammation of the bladder and blood in the urine that is severe enough that they need to be hospitalized for medical treatment or surgery. Your healthcare provider will check you for these problems during treatment with JEVTANA. Your healthcare provider may stop your treatment with JEVTANA for a short time, or permanently, if you develop inflammation of the bladder and bleeding that is severe. Tell your healthcare provider if you have blood in your urine, burning or pain during urination, or frequent or urgent need to urinate.
- Lung or breathing problems. Lung or breathing problems may happen with JEVTANA and may lead to death. Men who have lung disease before receiving JEVTANA may have a higher risk for developing lung or breathing problems with JEVTANA treatment. Your healthcare provider will check you for this problem and treat you if needed.
  Tell your healthcare provider right away if you develop any new or worsening symptoms, including trouble breathing, shortness of breath, chest pain, cough or fever.

What is JEVTANA?
JEVTANA is a prescription medicine used with the steroid medicine prednisone. JEVTANA is used to treat men with castration-resistant prostate cancer (prostate cancer that is resistant to medical or surgical treatments that lower testosterone) that has spread to other parts of the body, and that has worsened (progressed) after treatment with other medicines that included docetaxel.
It is not known if JEVTANA is safe and effective in females or children.

Who should not receive JEVTANA?
Do not receive JEVTANA if:

- your white blood cell (neutrophil count) is too low
- you have had a severe allergic reaction to cabazitaxel or other medicines that contain polysorbate 80. Ask your healthcare provider if you are not sure.
- you have severe liver problems

Before receiving JEVTANA, tell your healthcare provider about all your medical conditions, including if you:

- are over the age of 65
- had allergic reactions in the past
- have kidney or liver problems
- have lung problems
- are pregnant or plan to become pregnant. JEVTANA can cause harm to your unborn baby and loss of pregnancy (miscarriage).
- are a male with a female partner who is able to become pregnant. Males should use effective birth control (contraception) during treatment with JEVTANA and for 4 months after the last dose of JEVTANA.

Tell your healthcare provider about all the medicines you take, including prescription and over-the-counter medicines, vitamins, and herbal supplements.
JEVTANA can interact with many other medicines. Do not take any new medicines without asking your healthcare provider first. Your healthcare provider will tell you if it is safe to take the new medicine with JEVTANA.

How will I receive JEVTANA?

- JEVTANA will be given to you by an intravenous (IV) infusion into your vein.
- Your treatment will take about 1 hour.
- JEVTANA is usually given every 3 weeks. Your healthcare provider will decide how often you will receive JEVTANA.
- Your healthcare provider will also prescribe another medicine called prednisone for you to take by mouth every day during treatment with JEVTANA.
- Your healthcare provider will tell you how and when to take your prednisone.
- It is important that you take prednisone exactly as prescribed by your healthcare provider. If you forget to take your prednisone, or do not take it on schedule, make sure to tell your healthcare provider or nurse.
- Before each infusion of JEVTANA, you may receive other medicines to prevent or treat side effects.

What are the possible side effects of JEVTANA?
JEVTANA may cause serious side effects including:
The most common side effects of JEVTANA include:

- Low red blood cell count (anemia). Low red blood cell count is common with JEVTANA, but can sometimes also be serious. Your healthcare provider will regularly check your red blood cell count. Symptoms of anemia include shortness of breath and tiredness.
- Low blood platelet count. Low platelet count is common with JEVTANA, but can sometimes also be serious. Tell your healthcare provider if you have any unusual bruising or bleeding.

- diarrhea
- nausea
- tiredness
- weakness
- vomiting

- constipation
- decreased appetite
- back pain
- stomach (abdominal) pain

JEVTANA may cause fertility problems in males. This may affect your ability to father a child. Talk to your healthcare provider if you have concerns about fertility.
Tell your healthcare provider if you have any side effect that bothers you or that does not go away.
These are not all of the possible side effects of JEVTANA. For more information, ask your healthcare provider or pharmacist.
Call your doctor for medical advice about side effects. You may report side effects to FDA at 1-800-FDA-1088.

General information about the safe and effective use of JEVTANA.
Medicines are sometimes prescribed for purposes other than those listed in a Patient Information leaflet. You can ask your pharmacist or healthcare provider for information about JEVTANA that is written for health professionals.

What are the ingredients in JEVTANA?
Active ingredient: cabazitaxel
Inactive ingredients: polysorbate 80, citric acid monohydrate
Manufactured by: sanofi-aventis U.S. LLC, Morristown, NJ 07960 A SANOFI COMPANY
JEVTANA is a registered trademark of sanofi-aventis. ©2023 sanofi-aventis U.S. LLC
For more information, go to www.sanofi-aventis.us or call 1-800-633-1610.

This Patient Information has been approved by the U.S. Food and Drug Administration.

Revised: May 2025

PRINCIPAL DISPLAY PANEL - Kit Carton

NDC 0024-5824-11

Rx only

JEVTANA®
(cabazitaxel)
Injection

60 mg/1.5 mL Before First Dilution*

FOR INTRAVENOUS INFUSION ONLY AFTER SECOND DILUTION
*Requires two dilutions before administration. See back panel for details.

Warning: Cytotoxic Agent

Carton Contains:
One single-dose JEVTANA vial
One single-dose Diluent vial

sanofi